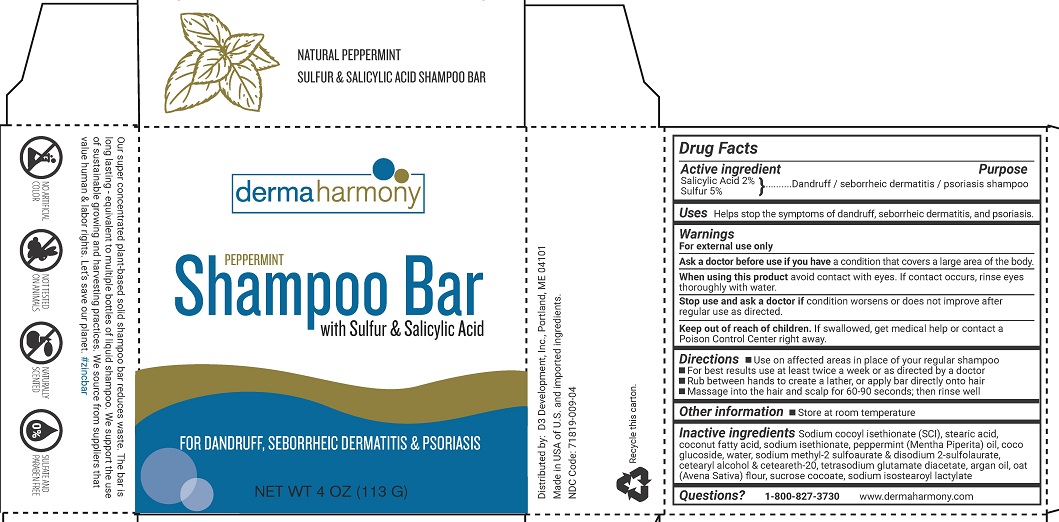 DRUG LABEL: Dermaharmony Bar
NDC: 71819-009 | Form: SHAMPOO
Manufacturer: D3 Development, Inc.
Category: otc | Type: HUMAN OTC DRUG LABEL
Date: 20241220

ACTIVE INGREDIENTS: SULFUR 5 g/100 g; SALICYLIC ACID 2 g/100 g
INACTIVE INGREDIENTS: CETOSTEARYL ALCOHOL; WATER; ARGAN OIL; SODIUM ISETHIONATE; POLYOXYL 20 CETOSTEARYL ETHER; COCONUT ACID; PEPPERMINT OIL; COCO GLUCOSIDE; SODIUM METHYL 2-SULFOLAURATE; DISODIUM 2-SULFOLAURATE; TETRASODIUM GLUTAMATE DIACETATE; OATMEAL; SODIUM ISOSTEAROYL LACTYLATE; SUCROSE COCOATE; STEARIC ACID; SODIUM COCOYL ISETHIONATE

Dermaharmony Sulfur and Salicylic Acid Shampoo Bar

Drug Facts

Active ingredient

Salicylic Acid 2%

Sulfur 5%

Purpose

Dandruff / sebhorreic dermatitis / psoriasis shampoo

Uses

Helps stop the symptoms of dandruff, sebhorreic dermatitis, and psoriasis.

Warnings

For external use only

Ask a doctor before use if you havea condition that covers a large area of the body.

When using this product,avoid contact with eyes. If contact occurs, rinse eyes thoroughly with water.

Stop use and ask a doctor ifcondition worsens or does not improve after regular use as directed.

Keep out of reach of children.If swallowed, get medical help or contact a Poison Control Center right away.

Directions

- Use on affected areas in place of your regular shampoo
- For best results use at least twice a week or as directed by a doctor
- Rub between hands to create a lather, or apply bar directly onto hair
- Massage into the hair and scalp for 60-90 seconds; then rinse well

Other information

- Store at room temperature

Inactive ingredients

Sodium cocoyl isethionate (SCI), stearic acid, coconut fatty acid, sodium isethionate, peppermint (Mentha Piperita) oil, coco glucoside, water, sodium methyl 2 sulfolaurate & disodium-2-sulfolaurate, cetearyl alcohol & ceteareth-20, tetrasodium glutamate diacetate, argan oil, oat (Avena Sativa) flour, sucrose cocoate, sodium isostearoyl lactylate

Questions?

1-800-827-3730

www.dermaharmony.com

Distributed by:

D3 Development, Inc., Portland, ME 04101

Made in USA of U.S. and imported ingredients

NDC 71819-009-04

PACKAGE LABEL

dermaharmony

PEPPERMINT

Shampoo Barwith Sulfur & Salicylic Acid

FOR DANDRUFF, SEBORRHEIC DERMATITIS & PSORIASIS

NET WT 4 OZ (113 G)